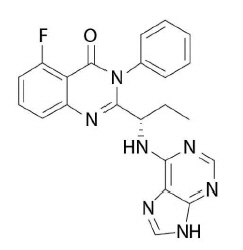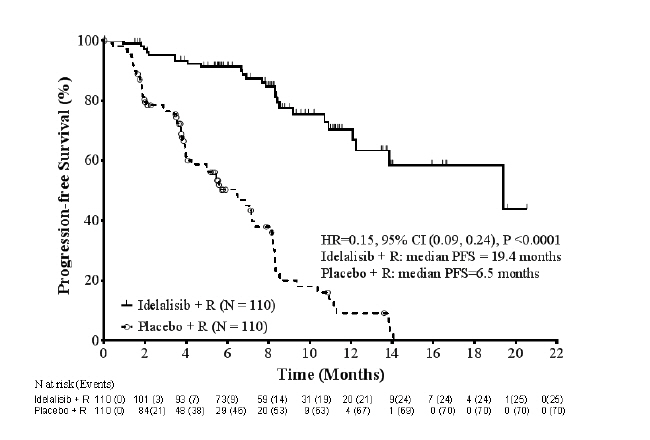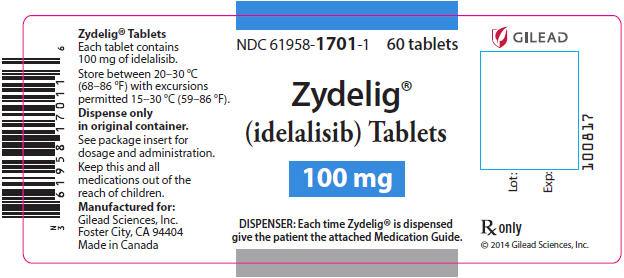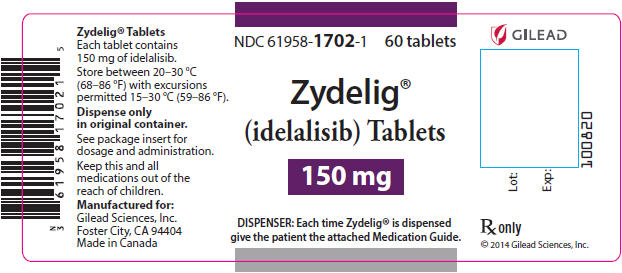 DRUG LABEL: Zydelig
NDC: 61958-1701 | Form: TABLET, FILM COATED
Manufacturer: Gilead Sciences, Inc.
Category: prescription | Type: HUMAN PRESCRIPTION DRUG LABEL
Date: 20250220

ACTIVE INGREDIENTS: IDELALISIB 100 mg/1 1
INACTIVE INGREDIENTS: MICROCRYSTALLINE CELLULOSE; HYDROXYPROPYL CELLULOSE (1600000 WAMW); SODIUM STARCH GLYCOLATE TYPE A POTATO; CROSCARMELLOSE SODIUM; MAGNESIUM STEARATE; POLYVINYL ALCOHOL, UNSPECIFIED; TITANIUM DIOXIDE; POLYETHYLENE GLYCOL, UNSPECIFIED; TALC; FD&C YELLOW NO. 6; ALUMINUM OXIDE

HIGHLIGHTS OF PRESCRIBING INFORMATION

These highlights do not include all the information needed to use ZYDELIG safely and effectively. See full prescribing information for ZYDELIG.
ZYDELIG® (idelalisib) tablets, for oral use
Initial U.S. Approval: 2014

WARNING: FATAL AND SERIOUS TOXICITIES: HEPATIC, SEVERE DIARRHEA, COLITIS, PNEUMONITIS, INFECTIONS, and INTESTINAL PERFORATION

See full prescribing information for complete boxed warning.

- Fatal and/or serious hepatotoxicity occurred in 16% of Zydelig-treated patients. Monitor hepatic function prior to and during treatment. Interrupt and then reduce or discontinue Zydelig. (5.1)
- Fatal and/or serious and severe diarrhea or colitis occurred in 20% of Zydelig-treated patients. Monitor for the development of severe diarrhea or colitis. Interrupt and then reduce or discontinue Zydelig. (5.2)
- Fatal and/or serious pneumonitis occurred in 4% of Zydelig-treated patients. Monitor for pulmonary symptoms and bilateral interstitial infiltrates. Interrupt or discontinue Zydelig. (5.3)
- Fatal and/or serious infections occurred in 48% of Zydelig-treated patients. Monitor for signs and symptoms of infection. Interrupt Zydelig if infection is suspected. (5.4)
- Fatal and serious intestinal perforation can occur in Zydelig-treated patients across clinical trials. Discontinue Zydelig if intestinal perforation is suspected. (5.5)

RECENT MAJOR CHANGES

Indications and Usage, Relapsed Follicular B-cell non-Hodgkin Lymphoma – Accelerated Approval Indication Removed (1)
2/2022

Indications and Usage, Relapsed Small Lymphocytic Lymphoma – Accelerated Approval Indication Removed (1)
2/2022

1 INDICATIONS AND USAGE

Zydelig is a kinase inhibitor indicated for the treatment of patients with:

- Relapsed chronic lymphocytic leukemia (CLL), in combination with rituximab, in patients for whom rituximab alone would be considered appropriate therapy due to other co-morbidities. (1)

Limitations of use:

Zydelig is not indicated and is not recommended for first-line treatment of any patient, including patients with CLL, small lymphocytic lymphoma (SLL), follicular lymphoma (FL), and other indolent non-Hodgkin lymphomas. (1, 6.1)

Zydelig is not indicated and is not recommended in combination with bendamustine and rituximab, or in combination with rituximab for the treatment of patients with FL, SLL, and other indolent non-Hodgkin lymphomas. (6.1)

2 DOSAGE AND ADMINISTRATION

Recommended dosage: 150 mg orally twice daily. (2.1)

3 DOSAGE FORMS AND STRENGTHS

Tablets: 100 mg, 150 mg. (3)

4 CONTRAINDICATIONS

History of serious hypersensitivity reactions to idelalisib, including anaphylaxis, or history of toxic epidermal necrolysis with any drug. (4)

5 WARNINGS AND PRECAUTIONS

- Severe Cutaneous Reactions: Monitor patients for the development of severe cutaneous reactions. Permanently discontinue Zydelig if confirmed. (2.2, 5.6)
- Hypersensitivity Reactions: Permanently discontinue Zydelig and institute appropriate supportive measures. (2.2, 5.7)
- Neutropenia: Monitor blood counts. Interrupt Zydelig until resolution and resume at reduced dose. (2.2, 5.8)
- Embryo-fetal Toxicity: May cause fetal harm. Advise females of reproductive potential of potential risk to a fetus and to use effective contraception. (5.9, 8.1, 8.3)

6 ADVERSE REACTIONS

- The most common adverse reactions (incidence ≥30%) in patients treated with Zydelig in combination trials are diarrhea, pneumonia, pyrexia, fatigue, rash, cough, and nausea. (6.1)
- Common laboratory abnormalities are neutropenia, ALT elevations and AST elevations. (6.1)

To report SUSPECTED ADVERSE REACTIONS, contact Gilead Sciences, Inc. at 1-800-GILEAD-5 or FDA at 1-800-FDA-1088 or www.fda.gov/medwatch.

7 DRUG INTERACTIONS

- Strong CYP3A Inhibitors: Additional monitoring required if alternative therapy is not available. (7.1)
- Strong CYP3A Inducers: Avoid coadministration of strong CYP3A inducers. (7.1)
- CYP3A Substrates: Avoid coadministration of sensitive CYP3A substrates. (7.2)

8 USE IN SPECIFIC POPULATIONS

Lactation: Advise not to breastfeed. (8.2)

FULL PRESCRIBING INFORMATION

WARNING: FATAL AND SERIOUS TOXICITIES: HEPATIC, SEVERE DIARRHEA, COLITIS, PNEUMONITIS, INFECTIONS, and INTESTINAL PERFORATION

Fatal and/or serious hepatotoxicity occurred in 16% of Zydelig-treated patients. Monitor hepatic function prior to and during treatment. Interrupt and then reduce or discontinue Zydelig as recommended [see Dosage and Administration (2.2), Warnings and Precautions (5.1)].

Fatal and/or serious and severe diarrhea or colitis occurred in 20% of Zydelig-treated patients. Monitor for the development of severe diarrhea or colitis. Interrupt and then reduce or discontinue Zydelig as recommended [see Dosage and Administration (2.2), Warnings and Precautions (5.2)].

Fatal and/or serious pneumonitis occurred in 4% of Zydelig-treated patients. Monitor for pulmonary symptoms and bilateral interstitial infiltrates. Interrupt or discontinue Zydelig as recommended [see Dosage and Administration (2.2), Warnings and Precautions (5.3)].

Fatal and/or serious infections occurred in 48% of Zydelig-treated patients. Monitor for signs and symptoms of infection. Interrupt Zydelig if infection is suspected [see Dosage and Administration (2.2), Warnings and Precautions (5.4)].

Fatal and serious intestinal perforation can occur in Zydelig-treated patients across clinical trials. Discontinue Zydelig for intestinal perforation [see Warnings and Precautions (5.5)].

1 INDICATIONS AND USAGE

Zydelig is indicated, in combination with rituximab, for the treatment of patients with relapsed chronic lymphocytic leukemia (CLL) for whom rituximab alone would be considered appropriate therapy due to other co-morbidities.

Limitations of Use

Zydelig is not indicated and is not recommended for first-line treatment of any patient, including patients with CLL, small lymphocytic lymphoma (SLL), follicular lymphoma (FL), and other indolent non-Hodgkin lymphomas.

Zydelig is not indicated and is not recommended in combination with bendamustine and rituximab, or in combination with rituximab for the treatment of patients with FL, SLL, and other indolent non-Hodgkin lymphomas.

2 DOSAGE AND ADMINISTRATION

2.1 Recommended Dosage

The recommended dosage of Zydelig is 150 mg administered orally twice daily with or without food until disease progression or unacceptable toxicity. The optimal and safe dosing regimen for patients who receive treatment longer than several months is unknown.

Swallow tablets whole.

If a planned dose of Zydelig is missed by less than 6 hours, take the missed dose as soon as possible and take the next dose as usual. If a dose of Zydelig is missed by more than 6 hours, skip the missed dose and take the next dose at the usual time.

2.2 Dosage Modifications for Adverse Reactions

Table 1 presents the dosage modification for specific adverse reactions.

For other severe or life-threatening adverse reactions, withhold Zydelig until resolution. If resuming Zydelig after interruption for other severe or life-threatening toxicities, reduce the dosage to 100 mg orally twice daily. Permanently discontinue Zydelig for recurrence of other severe or life-threatening Zydelig-related toxicity upon rechallenge.

Table 1 Dosage Modifications for Adverse Reactions
ALT/AST | >3–5 × ULN | >5–20 × ULN | >20 × ULN
[see Warnings and Precautions (5.1)] | Maintain Zydelig dose. Monitor at least weekly until ≤1 × ULN. | Withhold Zydelig. Monitor at least weekly until ALT/AST are ≤1 × ULN, then may resume Zydelig at 100 mg BID. | Discontinue Zydelig permanently.
Bilirubin | >1.5–3 × ULN | >3–10 × ULN | >10 × ULN
[see Warnings and Precautions (5.1)] | Maintain Zydelig dose. Monitor at least weekly until ≤1 × ULN. | Withhold Zydelig. Monitor at least weekly until bilirubin is ≤1 × ULN, then may resume Zydelig at 100 mg BID. | Discontinue Zydelig permanently.
Diarrhea [Moderate diarrhea: increase of 4–6 stools per day over baseline; severe diarrhea: increase of ≥7 stools per day over baseline.] | Moderate diarrhea | Severe diarrhea or hospitalization | Life-threatening diarrhea
[see Warnings and Precautions (5.2)] | Maintain Zydelig dose. Monitor at least weekly until resolved. | Withhold Zydelig. Monitor at least weekly until resolved, then may resume Zydelig at 100 mg BID. | Discontinue Zydelig permanently.
Pneumonitis | Any symptomatic pneumonitis
[see Warnings and Precautions (5.3)] | Discontinue Zydelig in patients with any severity of symptomatic pneumonitis.
Infections | Grade 3 or higher sepsis or pneumonia
[see Warnings and Precautions (5.4)] | Interrupt Zydelig until infection has resolved.
[see Warnings and Precautions (5.4)] | Evidence of CMV infection or viremia
[see Warnings and Precautions (5.4)] | Interrupt Zydelig in patients with evidence of active CMV infection of any grade or viremia (positive PCR or antigen test) until the viremia has resolved. If Zydelig is resumed, monitor patients by PCR or antigen test for CMV reactivation at least monthly.
[see Warnings and Precautions (5.4)] | Evidence of PJP infection
[see Warnings and Precautions (5.4)] | Interrupt Zydelig in patients with suspected PJP infection of any grade. Permanently discontinue Zydelig if PJP infection is confirmed.
Intestinal Perforation | Evidence of intestinal perforation
[see Warnings and Precautions (5.5)] | Permanently discontinue Zydelig in patients who experience intestinal perforation.
Severe Cutaneous Reactions | Suspected/Confirmed SJS, TEN, DRESS, or other severe or life-threatening (Grade ≥3) cutaneous reactions
[see Warnings and Precautions (5.6)] | Interrupt Zydelig in patients with suspected SJS, TEN, or DRESS until the etiology of the reaction has been determined. Permanently discontinue Zydelig in patients with confirmed SJS, TEN, or DRESS, or other severe or life-threatening (Grade ≥3) cutaneous reactions.
Hypersensitivity Reactions | Evidence of hypersensitivity reactions
[see Warnings and Precautions (5.7)] | Permanently discontinue Zydelig in patients who develop serious hypersensitivity reactions.
Neutropenia | ANC 1.0 to <1.5 Gi/L | ANC 0.5 to <1.0 Gi/L | ANC <0.5 Gi/L
[see Warnings and Precautions (5.8)] | Maintain Zydelig dose. | Maintain Zydelig dose. Monitor ANC at least weekly. | Interrupt Zydelig. Monitor ANC at least weekly until ANC ≥0.5 Gi/L, then may resume Zydelig at 100 mg BID.
Thrombocytopenia | Platelets 50 to <75 Gi/L | Platelets 25 to <50 Gi/L | Platelets <25 Gi/L
[see Adverse Reactions (6.1)] | Maintain Zydelig dose. | Maintain Zydelig dose. Monitor platelet counts at least weekly. | Interrupt Zydelig. Monitor platelet count at least weekly. May resume Zydelig at 100 mg BID when platelets ≥25 Gi/L.
Abbreviations: ANC: absolute neutrophil count; ALT, alanine aminotransferase; AST, aspartate aminotransferase; BID, twice daily; ULN, upper limit of normal; CMV, cytomegalovirus; DRESS, drug reaction with eosinophilia and systemic symptoms; PCR: polymerase chain reaction; PJP: Pneumocystis jirovecii pneumonia; SJS: Stevens-Johnson syndrome; TEN: toxic epidermal necrolysis

No dosage modification is recommended for lymphocytosis, which has been observed in some patients taking Zydelig. This observed lymphocytosis is a pharmacodynamic effect and should not be considered progressive disease in the absence of other clinical findings.

3 DOSAGE FORMS AND STRENGTHS

Tablets:

- 100 mg: orange, oval-shaped, film-coated tablet debossed with "GSI" on one side and "100" on the other side.
- 150 mg: pink, oval-shaped, film-coated tablet debossed with "GSI" on one side and "150" on the other side.

4 CONTRAINDICATIONS

Zydelig is contraindicated in patients with a history of serious hypersensitivity reactions to idelalisib, including anaphylaxis, or patients with a history of toxic epidermal necrolysis with any drug [see Warnings and Precautions (5.6, 5.7)] .

5 WARNINGS AND PRECAUTIONS

5.1 Hepatotoxicity

Fatal and/or serious hepatotoxicity occurred in 16% of patients treated with Zydelig in combination with rituximab or with unapproved combination therapies. Elevations in ALT or AST greater than 5 times the upper limit of normal have occurred [see Adverse Reactions (6.1)]. These findings were generally observed within the first 12 weeks of treatment and were reversible with dose interruption. After resumption of treatment at a lower dose, 26% of patients had recurrence of ALT and AST elevations. Discontinue Zydelig for recurrent hepatotoxicity.

Avoid concurrent use of Zydelig with other drugs that may cause liver toxicity.

Monitor ALT and AST in all patients every 2 weeks for the first 3 months of treatment, every 4 weeks for the next 3 months, then every 1 to 3 months thereafter. Monitor weekly for liver toxicity if the ALT or AST rises above 3 times the upper limit of normal until resolved. Withhold Zydelig if the ALT or AST is greater than 5 times the upper limit of normal, and continue to monitor AST, ALT and total bilirubin weekly until the abnormality is resolved [see Dosage and Administration (2.2)].

5.2 Severe Diarrhea or Colitis

Severe diarrhea or colitis (Grade 3 or higher) occurred in 20% of patients treated with Zydelig in combination with rituximab or with unapproved combination therapies [see Adverse Reactions (6.1)]. Diarrhea can occur at any time. Avoid concurrent use of Zydelig and other drugs that cause diarrhea. Diarrhea due to Zydelig responds poorly to antimotility agents. Median time to resolution ranged between 1 week and 1 month across trials, following interruption of Zydelig therapy and in some instances, use of corticosteroids [see Dosage and Administration (2.2)].

5.3 Pneumonitis

Fatal and serious pneumonitis occurred in patients treated with Zydelig [see Adverse Reactions (6.1)]. Clinical manifestations included interstitial infiltrates and organizing pneumonia. In randomized clinical trials of combination therapies, pneumonitis occurred in 4% of patients treated with Zydelig compared to 1% on the comparator arms. Time to onset of pneumonitis ranged from <1 to 15 months. Monitor patients on Zydelig for pulmonary symptoms. In patients taking Zydelig who present with pulmonary symptoms such as cough, dyspnea, hypoxia, interstitial infiltrates on a radiologic exam, or a decline by more than 5% in oxygen saturation, interrupt Zydelig until the etiology has been determined.

If symptomatic pneumonitis or organizing pneumonia is diagnosed, initiate appropriate treatment with corticosteroids and permanently discontinue Zydelig [see Dosage and Administration (2.2)].

5.4 Infections

Fatal and/or serious infections occurred in 48% of patients treated with Zydelig in combination with rituximab or with unapproved combination therapies [see Adverse Reactions (6.1)]. The most common infections were pneumonia, sepsis, and febrile neutropenia. Treat infections prior to initiation of Zydelig therapy. Monitor patients on Zydelig for signs and symptoms of infection, and interrupt Zydelig for Grade 3 or higher infection [see Dosage and Administration (2.2)].

Serious or fatal Pneumocystis jirovecii pneumonia (PJP) or cytomegalovirus (CMV) occurred in <1% of patients treated with Zydelig. Provide PJP prophylaxis during treatment with Zydelig. Interrupt Zydelig in patients with suspected PJP infection of any grade, and permanently discontinue Zydelig if PJP infection of any grade is confirmed. Regular clinical and laboratory monitoring for CMV infection is recommended in patients with history of CMV infection or positive CMV serology at the start of treatment with Zydelig. Interrupt Zydelig in the setting of positive CMV PCR or antigen test until the viremia has resolved. If Zydelig is subsequently resumed, patients should be monitored by PCR or antigen test for CMV reactivation at least monthly [see Dosage and Administration (2.2)].

5.5 Intestinal Perforation

Fatal and serious intestinal perforation occurred in Zydelig-treated patients. At the time of perforation, some patients had moderate to severe diarrhea. Advise patients to promptly report any new or worsening abdominal pain, chills, fever, nausea, or vomiting. Discontinue Zydelig permanently in patients who experience intestinal perforation.

5.6 Severe Cutaneous Reactions

Fatal cases of Stevens-Johnson syndrome (SJS) and toxic epidermal necrolysis (TEN) have occurred in patients treated with Zydelig. Cases of drug reaction with eosinophilia and systemic symptoms (DRESS) have also occurred [see Adverse Reactions (6.2)]. Zydelig is contraindicated in patients with a history of toxic epidermal necrolysis [see Contraindications (4)]. If SJS, TEN, or DRESS is suspected, interrupt Zydelig until the etiology of the reaction has been determined. If SJS, TEN, or DRESS is confirmed, permanently discontinue Zydelig [see Dosage and Administration (2.2)].

Other severe or life-threatening (Grade ≥3) cutaneous reactions, including dermatitis exfoliative, rash, rash erythematous, rash generalized, rash macular, rash maculo-papular, rash papular, rash pruritic, exfoliative rash, and skin disorder, have been reported in patients treated with Zydelig. Monitor patients for the development of other severe or life-threatening cutaneous reactions and permanently discontinue Zydelig [see Dosage and Administration (2.2)].

5.7 Hypersensitivity Reactions

Serious hypersensitivity reactions, including anaphylaxis, have been reported in patients on Zydelig. Zydelig is contraindicated in patients with a history of serious hypersensitivity reactions to idelalisib, including anaphylaxis [see Contraindications (4)]. In patients who develop serious hypersensitivity reactions, permanently discontinue Zydelig [see Dosage and Administration (2.2)] and institute appropriate supportive measures.

5.8 Neutropenia

Grade 3 or 4 neutropenia occurred in 58% of patients treated with Zydelig in combination with rituximab or with unapproved combination therapies [see Adverse Reactions (6.1)]. Monitor blood counts at least every 2 weeks for the first 6 months of therapy, and at least weekly in patients while neutrophil counts are less than 1.0 Gi/L. Interrupt Zydelig until resolution and resume at reduced dose [see Dosage and Administration (2.2)].

5.9 Embryo-fetal Toxicity

Based on findings in animals and its mechanism of action, Zydelig may cause fetal harm when administered to a pregnant woman. In animal reproduction studies, administration of idelalisib to pregnant rats during organogenesis caused decreased fetal weight and congenital malformations at systemic exposures 12 times those reported in patients at the recommended dose of 150 mg twice daily.

Advise pregnant women of the potential risk to a fetus. Advise females of reproductive potential to use effective contraception during treatment with Zydelig and for 1 month after the last dose [see Use in Specific Populations (8.1, 8.3)].

6 ADVERSE REACTIONS

The following clinically significant adverse reactions are described elsewhere in the labeling.

- Hepatotoxicity [see Warnings and Precautions (5.1)]
- Severe Diarrhea or Colitis [see Warnings and Precautions (5.2)]
- Pneumonitis [see Warnings and Precautions (5.3)]
- Infections [see Warnings and Precautions (5.4)]
- Intestinal Perforation [see Warnings and Precautions (5.5)]
- Severe Cutaneous Reactions [see Warnings and Precautions (5.6)]
- Hypersensitivity Reactions [see Warnings and Precautions (5.7)]
- Neutropenia [see Warnings and Precautions (5.8)]

6.1 Clinical Trials Experience

Because clinical trials are conducted under widely varying conditions, adverse reaction rates observed in the clinical trials of a drug cannot be directly compared to rates in the clinical trials of another drug and may not reflect the rates observed in practice.

The pooled safety population described in the WARNINGS AND PRECAUTIONS reflect exposure to Zydelig at a dosage of 150 mg twice daily in 110 patients administered in combination with rituximab in Study 312-0116, and in combination with other drugs in 380 patients. Among 490 patients who received Zydelig, 74% were exposed for 6 months or longer and 50% were exposed for one year or longer. In this pooled safety population, the most common (> 30%) adverse reactions were diarrhea, pneumonia, pyrexia, fatigue, rash, cough, and nausea. Common laboratory abnormalities were neutropenia, ALT elevations and AST elevations.

Summary of Clinical Trials in Chronic Lymphocytic Leukemia

The safety data reflect exposure to Zydelig from two randomized, double-blind clinical trials (Studies 312-0116 and 312-0115) in 634 patients with relapsed CLL [see Clinical Studies (14.1)] and one randomized, open-label trial in 259 patients with relapsed CLL (Study 312-0119).

Zydelig with Rituximab (Study 312-0116)

Patients with relapsed CLL received up to 8 doses of rituximab (R) with (n=110) or without Zydelig (n=108)150 mg twice daily. The median duration of exposure to Zydelig was 8 months.

Serious adverse reactions were reported in 65 (59%) patients treated with Zydelig + R The most frequent serious adverse reactions reported for patients treated with Zydelig + R were pneumonia (23%), diarrhea (10%), pyrexia (9%), sepsis (8%), and febrile neutropenia (5%).

Adverse reactions that led to discontinuation of Zydelig occurred in 19 (17%) patients. The most common adverse reactions that led to treatment discontinuations were hepatotoxicity and diarrhea/colitis.

Forty-two (38%) patients had dose interruptions and sixteen (15%) patients had dose reductions due to adverse reactions or laboratory abnormalities. The most common reasons for dose interruptions or reductions were pneumonia, diarrhea or colitis, rash, and elevated transaminases.

Table 2 and Table 3 summarize common adverse reactions and laboratory abnormalities reported for Zydelig + R and placebo + R arms.

Table 2 Adverse Reactions Reported in ≥5% of Patients with CLL and Occurred at ≥2% Higher Incidence in Patients Receiving Zydelig in Study 312-0116
 | Zydelig + R N=110 (%) |  | Placebo + R N=108 (%)
Adverse Reaction | Any Grade | Grade ≥3 | Any Grade | Grade ≥3
General disorders and administration site conditions
pyrexia | 44 (40) | 3 (3) | 20 (19) | 1 (1)
chills | 27 (25) | 2 (2) | 17 (16) | 0
pain | 8 (7) | 0 | 1 (1) | 0
Gastrointestinal disorders
diarrhea [Diarrhea includes the following preferred terms: diarrhea, colitis.] | 35 (32) | 12 (11) | 20 (19) | 0
nausea | 30 (27) | 1 (1) | 25 (23) | 0
abdominal pain [Abdominal pain includes the following preferred terms: abdominal pain, abdominal pain upper, abdominal pain lower.] | 20 (18) | 1 (1) | 17 (16) | 2 (2)
vomiting | 17 (15) | 0 | 9 (8) | 0
gastroesophageal reflux disease | 11 (10) | 1 (1) | 0 | 0
stomatitis | 7 (6) | 2 (2) | 1 (1) | 0
Respiratory, thoracic, and mediastinal disorders
pneumonia [Pneumonia includes the terms: pneumonia, pneumonitis, lung infection, lung infiltration, pneumocystis jiroveci pneumonia, pneumonia legionella, lung infection pseudomonal, pneumonia fungal, respiratory tract infection, lower respiratory tract infection, and lower respiratory tract infection bacterial.] | 33 (30) | 23 (21) | 20 (19) | 14 (13)
Skin and subcutaneous tissue disorders
rash [Rash includes the following preferred terms: dermatitis exfoliative, drug eruption, rash, rash erythematous, rash generalized, rash macular, rash maculo-papular, rash papular, rash pruritic, rash morbilliform, and exfoliative rash.] | 27 (25) | 4 (4) | 7 (6) | 1 (1)
Metabolism and Nutrition Disorders
decreased appetite | 18 (16) | 2 (2) | 12 (11) | 2 (2)
dehydration | 7 (6) | 3 (3) | 0 | 0
Infections and infestations
sepsis [Sepsis includes the terms: sepsis, septic shock, neutropenic sepsis, and sepsis syndrome] | 10 (9) | 10 (9) | 4 (4) | 4 (4)
sinusitis | 9 (8) | 0 | 6 (6) | 0
urinary tract infection | 9 (8) | 1 (1) | 4 (4) | 2 (2)
bronchitis | 8 (7) | 1 (1) | 5 (5) | 1 (1)
oral herpes | 6 (5) | 1 (1) | 3 (3) | 0
Psychiatric disorders
insomnia | 10 (9) | 0 | 7 (6) | 0
Musculoskeletal and connective tissue disorders
arthralgia | 9 (8) | 1 (1) | 4 (4) | 0
Nervous system disorders
lethargy | 6 (5) | 0 | 2 (2) | 0

Table 3 Hematologic and Hepatic Laboratory Abnormalities Reported in ≥10% of Patients with CLL and Occurred at ≥5% Higher Incidence in Patients Receiving Zydelig in Study 312-0116
 | Zydelig + R N=110 (%) |  | Placebo + R N=108 (%)
Laboratory Parameter | Any Grade | Grade 3–4 | Any Grade | Grade 3–4
Hematology abnormalities
neutropenia | 71 (65) | 46 (42) | 61 (56) | 33 (31)
leukopenia | 34 (31) | 9 (8) | 25 (23) | 9 (8)
lymphocytopenia | 23 (21) | 11 (10) | 13 (12) | 4 (4)
Serum chemistry abnormalities
ALT increased | 43 (39) | 10 (9) | 13 (12) | 1 (1)
AST increased | 31 (28) | 6 (5) | 16 (15) | 0

After closure of Study 312-0116, 71 patients continued treatment with Zydelig on an extension study (Study 312-0117). The median duration of exposure was 18 months. Serious adverse reactions occurred in 48 (68%) patients. The most frequent serious adverse reactions reported were pneumonia (30%), diarrhea (15%), and pyrexia (11%).

The most frequent adverse reactions were pneumonia (51%), pyrexia (46%), and cough (45%). The most frequent Grade 3 or greater adverse reactions were pneumonia (30%), diarrhea (15%), and sepsis (10%).

Zydelig with Ofatumumab (Study 312-0119)

In Study 312-0119, 259 patients with relapsed CLL received up to 12 doses of ofatumumab with or without Zydelig 150 mg orally twice daily. Zydelig in combination with ofatumumab is not indicated for the treatment of relapsed CLL. The median duration of exposure to Zydelig was 13.9 months.

Serious adverse reactions were reported in 133 (77%) patients treated with Zydelig + ofatumumab. The most frequent serious adverse reactions reported were pneumonia (14%), pyrexia (13%), and diarrhea (12%).

Adverse reactions that led to discontinuation of Zydelig occurred in 71 (41%) patients.

One hundred and ten (64%) patients had dose interruptions and 42 (24%) patients had dose reductions due to adverse reactions or laboratory abnormalities. The most common reasons for dose discontinuations, reductions, or interruptions were diarrhea and colitis.

The most common adverse reactions were diarrhea (55%), pyrexia (38%), nausea (34%), and fatigue (34%).

Zydelig with Bendamustine and Rituximab (Study 312-0115)

In Study 312-0115, patients with relapsed CLL received up to 6 cycles of bendamustine and rituximab (BR) with or without Zydelig 150 mg orally twice daily. Zydelig in combination with bendamustine and rituximab is not indicated for the treatment of relapsed CLL. The median duration of exposure to Zydelig was 18.2 months.

Serious adverse reactions were reported in 147 (71%) patients treated with Zydelig + BR. The most frequent serious adverse reactions reported for patients treated with Zydelig + BR were febrile neutropenia (21%), pneumonia (17%), pyrexia (12%), and diarrhea (6%).

Adverse reactions that led to discontinuation of Zydelig occurred in 68 (33%) patients. The most common adverse reactions that led to treatment discontinuations were pneumonia, diarrhea, and pyrexia.

One hundred twenty-two (59%) patients treated with Zydelig + BR had dose interruptions and 34 (16%) patients had dose reductions due to adverse reactions. The most common reasons for dose interruptions or reductions were increased ALT and diarrhea.

The most common adverse reactions were neutropenia (64%), pyrexia (43%), and diarrhea (41%).

Summary of Clinical Trials in Indolent Non-Hodgkin Lymphoma

The safety data reflect exposure to Zydelig from three open-label clinical trials (Studies 101-09, 101-02, and 101-10 in 146 patients with indolent non-Hodgkin lymphoma (iNHL) treated with Zydelig 150 mg orally twice daily. Zydelig is not indicated for the treatment of iNHL. The median duration of exposure was 6.1 months (range 0.3 to 26.4 months).

Serious adverse reactions were reported in 73 (50%) patients. The most frequent serious adverse reactions that occurred were pneumonia (15%), diarrhea (11%), and pyrexia (9%).

Adverse reactions resulted in interruption or discontinuation for 78 (53%) patients. The most common reasons for interruption or discontinuations were diarrhea (11%), pneumonia (11%), and elevated transaminases (10%).

The most common adverse reactions were neutropenia (53%), ALT increased (50%), diarrhea (47%), AST increased (41%), fatigue (30%), nausea and cough (29% each), anemia and pyrexia (28% each), abdominal pain and thrombocytopenia (26% each), and pneumonia (25%).

Summary of Discontinued Clinical Trials in Indolent Non-Hodgkin Lymphoma and First-Line CLL

Zydelig is not indicated for patients with indolent non-Hodgkin lymphoma or previously untreated CLL either as monotherapy or in combination with rituximab or BR. Safety data described below reflect exposure to Zydelig in three randomized, double-blind clinical trials (Studies 312-0123, 313-0124, and 313-0125) in patients with CLL and iNHL.

In Study 312-0123 (NCT01980888), 311 patients with previously untreated CLL received up to 6 cycles of BR with or without Zydelig 150 mg twice daily.

In Study 313-0124 (NCT01732913), 295 patients with previously treated iNHL [FL 66%, marginal zone lymphoma (MZL) 19%, SLL 9%, lymphoplasmacytic lymphoma (LPL)/Waldenstrom macroglobulinemia (WM) 6%] received 8 doses of R with or without Zydelig 150 mg twice daily. Patients had a median of one prior therapy.

In Study 313-0125 (NCT01732926), 475 patients with previously treated iNHL (FL 63%, MZL 15%, SLL 11%, LPL/WM 11%) received up to 6 cycles of BR with or without Zydelig 150 mg twice daily. Patients had a median of two prior therapies.

These three studies were terminated early due to a higher incidence of fatal and/or serious adverse reactions observed in patients treated with Zydelig in combination with R or BR. The most frequent serious adverse reactions were in the system organ classes of infections and infestations, blood and lymphatic system disorders, and gastrointestinal disorders.

6.2 Postmarketing Experience

The following adverse reactions have been identified during postapproval use of Zydelig. Because these reactions are reported voluntarily from a population of uncertain size, it is not always possible to reliably estimate their frequency or establish a causal relationship to drug exposure.

Skin and Subcutaneous Disorders - Stevens-Johnson syndrome (SJS), toxic epidermal necrolysis (TEN), and drug reaction with eosinophilia and systemic symptoms (DRESS)

7 DRUG INTERACTIONS

7.1 Effects of Other Drugs on Zydelig

Table 6 lists the potential effects of the coadministration of strong CYP3A modulators on Zydelig.

Table 6 Drug Interactions with Zydelig that affect Idelalisib Concentrations
Strong CYP3A Inhibitors
Clinical Impact | - Coadministration with strong CYP3A inhibitors may increase idelalisib concentrations [see Clinical Pharmacology (12.3)]. - Increased idelalisib concentrations may increase the risk of exposure related adverse reactions.
Prevention or Management | - Use other drugs that are not strong CYP3A inhibitors. - If unable to use alternative drugs, monitor patients more frequently for Zydelig adverse reactions [see Adverse Reactions (6.1)].
Strong CYP3A Inducers
Clinical Impact | - Coadministration with strong CYP3A inducers may decrease idelalisib concentrations [see Clinical Pharmacology (12.3)]. - Decreased idelalisib concentrations may reduce efficacy.
Prevention or Management | Avoid coadministration of Zydelig with strong CYP3A4 inducers.

7.2 Effects of Zydelig on Other Drugs

The coadministration of Zydelig with a CYP3A substrate may increase the concentrations of this CYP3A substrate. Avoid coadministration of Zydelig with sensitive CYP3A substrates [see Clinical Pharmacology (12.3)].

8 USE IN SPECIFIC POPULATIONS

8.1 Pregnancy

Risk Summary

Based on findings in animal studies and the mechanism of action [see Clinical Pharmacology (12.1)], Zydelig may cause fetal harm when administered to a pregnant woman.

There are no available data in pregnant women to inform the drug-associated risk. In animal reproduction studies, administration of idelalisib to pregnant rats during organogenesis resulted in decreased fetal weight and congenital malformations in rats at maternal exposures (AUC) 12 times those reported in patients at the recommended dosage of 150 mg twice daily (see Data).

The estimated background risk of major birth defects and miscarriage for the indicated populations is unknown. All pregnancies have a background risk of birth defect, loss, or other adverse outcomes. In the U.S. general population, the estimated background risk of major birth defects and miscarriage of clinically recognized pregnancies 2–4% and 15–20%, respectively.

Data

Animal Data

In an embryo-fetal development study in rats, pregnant animals receiving oral doses of idelalisib during the period of organogenesis (implantation to closure of the hard palate), embryo-fetal toxicities were observed at the mid- and high-doses that also resulted in maternal toxicity, based on reductions in maternal body weight gain. Adverse findings at idelalisib doses ≥ 75 mg/kg/day included decreased fetal weights, external malformations (short tail), and skeletal variations (delayed ossification and/or unossification of the skull, vertebrae, and sternebrae). Additional findings were observed at 150 mg/kg/day dose of idelalisib and included urogenital blood loss, complete resorption, increased post-implantation loss, and malformations (vertebral agenesis with anury, hydrocephaly, and microphthalmia/anophthalmia). The dose of 75 and 150 mg/kg/day of idelalisib in rats resulted in exposures (AUC) of approximately 12 and 30 times, respectively, the human exposure at the recommended dose of 150 mg twice daily.

8.2 Lactation

Risk Summary

There are no data on the presence of idelalisib or its metabolites in human milk or its effects on the breastfed child or on milk production. Because of the potential for serious adverse reactions in the breastfed child, advise women not to breastfeed during treatment with Zydelig and for 1 month after the last dose.

8.3 Females and Males of Reproductive Potential

Zydelig may cause fetal harm when administered to a pregnant woman [see Use in Specific Populations (8.1)].

Pregnancy

Pregnancy testing is recommended for females of reproductive potential prior to starting Zydelig.

Contraception

Females

Advise females of reproductive potential to use effective contraception during treatment with Zydelig and for 1 month after the last dose.

Males

Advise males with female partners of reproductive potential to use effective contraception during treatment with Zydelig and for 3 months after the last dose [see Nonclinical Toxicology (13.1)].

8.4 Pediatric Use

Safety and effectiveness of Zydelig in pediatric patients have not been established.

8.5 Geriatric Use

Of the 490 patients with relapsed CLL who were treated with Zydelig in combination trials, 271 (55%) were 65 years of age and older. When comparing patients 65 years of age or older to younger patients with CLL, older patients had a higher incidence of discontinuation due to an adverse reaction (36% vs 28%), higher incidence of serious adverse reactions (73% vs 67%), and higher incidence of death (13% vs 9%).

8.6 Hepatic Impairment

No dose adjustment is recommended for patients with ALT or AST or bilirubin > upper limit of normal (ULN); however, limited safety and efficacy data are available for patients with baseline AST or ALT > 2.5 × ULN or bilirubin > 1.5 × ULN. Monitor patients with baseline hepatic impairment for adverse reactions [see Warnings and Precautions (5)]. Follow dosage modifications for adverse reactions [see Dosage and Administration (2.2)].

11 DESCRIPTION

Idelalisib is a kinase inhibitor. The chemical name for idelalisib is 5-fluoro-3-phenyl-2-[(1S)-1-(9H-purin-6-ylamino)propyl]quinazolin-4(3H)-one. It has a molecular formula of C22H18FN7O and a molecular weight of 415.42 g/mol. Idelalisib has the following structural formula:

Idelalisib is a white to off-white solid with a pH-dependent aqueous solubility ranging from <0.1 mg/mL at pH 5–7 to over 1 mg/mL at pH 2 under ambient conditions.

Zydelig (idelalisib) tablets are for oral use. Each tablet contains either 100 mg or 150 mg of idelalisib with the following inactive ingredients: microcrystalline cellulose, hydroxypropyl cellulose, croscarmellose sodium, sodium starch glycolate, magnesium stearate and a tablet coating. The tablet coating consists of polyethylene glycol, talc, polyvinyl alcohol, and titanium dioxide and of FD&C Yellow #6/Sunset Yellow FCF Aluminum Lake (for the 100 mg tablet) and red iron oxide (for the 150 mg tablet).

12 CLINICAL PHARMACOLOGY

12.1 Mechanism of Action

Idelalisib is an inhibitor of phosphatidylinositol 3-kinase, PI3Kδ, which is expressed in normal and malignant B-cells. Idelalisib induced apoptosis and inhibited proliferation in cell lines derived from malignant B-cells and in primary tumor cells. Idelalisib inhibits several cell signaling pathways, including B-cell receptor (BCR) signaling and the CXCR4 and CXCR5 signaling, which are involved in trafficking and homing of B-cells to the lymph nodes and bone marrow. Treatment of lymphoma cells with idelalisib resulted in inhibition of chemotaxis and adhesion, and reduced cell viability.

12.2 Pharmacodynamics

Cardiac Electrophysiology

At a dose 2.7 times the maximum recommended dose, Zydelig did not prolong the QT/QTc interval (i.e., ≤10 ms).

12.3 Pharmacokinetics

Idelalisib exposure increased in a less than dose-proportional manner over a dose range of 50 mg to 350 mg twice daily (0.3 to 2.3 times the approved recommended dosage).

Following 150 mg twice daily administration of idelalisib, average (% coefficient of variation) maximum concentrations (Cmax) and area under the curve (AUC) at steady-state were 1861 (43%) ng/mL and 10598 (41%) ng∙h/mL for idelalisib.

Absorption

The median time to peak concentration (Tmax) was observed at 1.5 hours.

Food Effect

The administration of a single dose of Zydelig with a high-fat meal (900 calories: 525 calories fat, 250 calories carbohydrates, and 125 calories protein) increased idelalisib AUC 1.4-fold relative to fasting conditions.

Distribution

Protein binding of idelalisib is ≥ 84% with no concentration dependence.

The mean blood-to-plasma ratio was 0.7.

The apparent central volume of distribution at steady state is 23 L (%CV ~85%). Idelalisib is a substrate of P-glycoprotein (P-gp) and BCRP in vitro.

Elimination

The population apparent systemic clearance at steady-state is 14.9 L/hr (%CV ~ 38%). The population terminal elimination half-life of idelalisib is 8.2 hours.

Metabolism

Idelalisib is metabolized via aldehyde oxidase and CYP3A with additional minor metabolism by UGT1A4.

Excretion

Following a single 150 mg dose of radiolabeled idelalisib, 78% of the radioactivity was excreted in feces and 14% was excreted in the urine. Idelalisib is not a substrate of OATP1B1, OATP1B3, OAT1, OAT3, or OCT2.

Specific Populations

Age (18 to 91 years), sex, race (White, and non-Whites), renal impairment (creatinine clearance ≥ 15 mL/min) and weight (38 to 148 kg) had no effect on idelalisib exposure.

Patients with Hepatic Impairment

The mean AUC increased up to 1.7-fold in patients with hepatic impairment (defined as ALT or AST or bilirubin values ≥ ULN) compared to patients with normal hepatic function. There is limited information on idelalisib exposure in patients with baseline AST or ALT > 2.5 × ULN or bilirubin > 1.5 × ULN [see Specific Populations (8.6)].

Drug Interaction Studies

Effect of Other Drugs on Idelalisib

The coadministration of rifampin (strong CYP3A inducer and P-gp inducer) to healthy subjects decreased the mean idelalisib AUC by 75% and the mean Cmax by 58% [see Drug Interactions (7.1)].

The coadministration of ketoconazole (strong CYP3A inhibitor and P-gp inhibitor) to healthy subjects increased the mean idelalisib AUC by 1.8-fold. No changes in the mean Cmax were observed [see Drug Interactions (7.1)].

In vitro studies suggest that idelalisib inhibits CYP2C8, CYP2C19, and UGT1A1 and induces CYP2B6.

Effect of Idelalisib on Other Drugs

The mean Cmax of midazolam increased by 2.4-fold and the mean AUC of midazolam increased by 5.4-fold when midazolam (sensitive CYP3A substrate) was coadministered with Zydelig [see Drug Interactions (7.2)].

No changes in exposure to rosuvastatin (OATP1B1 and OATP1B3 substrate) or digoxin (P-glycoprotein substrate) were observed when coadministered with Zydelig.

13 NONCLINICAL TOXICOLOGY

13.1 Carcinogenesis, Mutagenesis, Impairment of Fertility

Idelalisib was not carcinogenic in a 26-week study in transgenic mice when administered daily by oral gavage at doses up to 500 mg/kg/day in males and 1000 mg/kg/day in females. Idelalisib was not carcinogenic in a 2-year study in rats when administered daily by oral gavage at exposures 0.40/0.62-fold (male/female), compared to the exposure in patients with hematologic malignancies administered the recommended dose of 150 mg twice daily.

Idelalisib did not induce mutations in the bacterial mutagenesis (Ames) assay and was not clastogenic in the in vitro chromosome aberration assay using human peripheral blood lymphocytes. Idelalisib was genotoxic in males in the in vivo rat micronucleus study at a high dose of 2000 mg/kg.

Idelalisib may impair fertility in humans. In a fertility study, treated male rats (25, 50, or 100 mg/kg/day of idelalisib) were mated with untreated females. Decreased epididymidal and testicular weights were observed at all dose levels and reduced sperm concentration at the mid- and high doses; however, there were no adverse effects on fertility parameters. The low dose in males resulted in an exposure (AUC) that is approximately 50% of the exposure in patients at the recommended dose of 150 mg twice daily.

In a separate fertility study, treated female rats (25, 50, or 100 mg/kg/day of idelalisib) were mated with untreated males. There were no adverse effects on fertility parameters; however, there was a decrease in the number of live embryos at the high dose. The high dose in females resulted in an exposure (AUC) that is approximately 17-fold the exposure in patients at the recommended dose of 150 mg twice daily.

13.2 Animal Toxicology and/or Pharmacology

Toxicities observed in animals and not reported in patients include cardiac toxicity (cardiomyopathy, inflammation, and increased heart weight) and pancreatic findings (inflammation, hemorrhage, and low-incidence acinar degeneration and hyperplasia). These findings were observed in Sprague-Dawley rats in toxicology studies at exposures (AUCs) higher than those reported in patients at the recommended dose of 150 mg twice daily. Cardiac inflammation was mainly seen in a 28-day study in rats, the other findings were observed in the 13-week and/or 6-month studies.

14 CLINICAL STUDIES

Zydelig was evaluated in a randomized, double-blind, placebo-controlled study GS-US-312-0116 (referred to as 312-0116) (NCT01539512) in 220 patients with relapsed CLL who required treatment and were unable to tolerate standard chemoimmunotherapy due to coexisting medical conditions, reduced renal function as measured by creatinine clearance < 60 mL/min, or NCI CTCAE Grade ≥ 3 neutropenia or Grade ≥ 3 thrombocytopenia resulting from myelotoxic effects of prior therapy with cytotoxic agents. Patients were randomized 1:1 to receive 8 doses of rituximab (first dose at 375 mg/m^2, subsequent doses at 500 mg/m^2 every 2 weeks for 4 infusions and every 4 weeks for an additional 4 infusions) in combination with either an placebo taken orally twice daily or with Zydelig 150 mg taken orally twice daily until disease progression or unacceptable toxicity.

The median age was 71 years (range 47, 92) with 78% over 65, 66% were male, and 90% were White. The median time since diagnosis was 8.5 years. The median number of prior therapies was 3. Nearly all (96%) patients had received prior anti-CD20 monoclonal antibodies. The most common (>15%) prior regimens were: bendamustine + rituximab (BR) (98 patients, 45%), fludarabine + cyclophosphamide + rituximab (75 patients, 34%), single-agent rituximab (67 patients, 31%), fludarabine + rituximab (37 patients, 17%), and chlorambucil (36 patients, 16%). The median CIRS (Cumulative Illness Rating Scale) score was 8 (range 0–17), and 85% of patients had a score of >6. Median Karnofsky score was 80. Median estimated Creatinine Clearance (eCLcr) was 63.6 mL/min, with 41% of patients having an eCLcr of <60 mL/min. At screening, 19.5% of patients had a platelet count of <50 × 10^9/L, and 13.2% had an absolute neutrophil count (ANC) of <1 × 10^9/L.

The efficacy of Zydelig was based on progression free survival (PFS), as assessed by an independent review committee (IRC). The trial was stopped for efficacy following the first pre-specified interim analysis. Results of a second interim analysis continued to show a statistically significant improvement for Zydelig + R compared to placebo + R for the major efficacy outcome measure of PFS (HR: 0.18, 95% CI [0.10, 0.32], p <0.0001).

At the final analysis, with a median follow-up of 8.3 months for the Zydelig + R group, and 5.6 months for the placebo + R group, the median PFS for the Zydelig + R group was 19.4 months (95% CI: 12.3, Not Reached) versus 6.5 months (95% CI: 4.0, 7.3) for the placebo + R group (HR: 0.15, 95% CI [0.09, 0.24], p < 0.0001).

Updated efficacy results are shown in Table 7 and the Kaplan-Meier curve for PFS is shown in Figure 1.

Table 7 Efficacy Results from Study 312-0116
 |  | Zydelig + R N = 110 | Placebo + R N = 110
PFS | Median (months) (95% CI) | 19.4 (12.3, NR) | 6.5 (4.0, 7.3)
 | Hazard ratio (95% CI) | 0.15 (0.09, 0.24)
 | P-value | < 0.0001 [The p value for PFS was based on stratified log-rank test.]
ORR [ORR defined as the proportion of patients who achieved a complete response (CR) or PR. All PRs achieved; none of the patients achieved a CR.] | (All PRs) | 92 (83.6%) | 17 (15.5%)
 | 95% CI | 75.4, 90.0 | 9.3, 23.6
 | Odds Ratio (95% CI) | 27.8 (13.4, 57.5)
 | P-value | <0.0001
DOR | Median (months) (95% CI) | NR (12, NR) | 6.2 (2.8, 6.5)
PFS: progression-free survival; NR: not reached; ORR: overall response rate; PR: partial response; DOR: duration of response

Figure 1 Kaplan-Meier Plot of IRC-Assessed PFS for Study 312-0116

16 HOW SUPPLIED/STORAGE AND HANDLING

Zydelig tablets supplied as follows:

Tablet Strength | Package Configuration | NDC No. | Description of Tablet; Debossed on Tablet
150 mg | High density polyethylene (HDPE) bottle with a polyester fiber coil, capped with a child-resistant closure. Each bottle contains 60 film-coated tablets. | 61958-1702-1 | Oval shaped; pink; "150" on one side and "GSI" on the other side
100 mg | High density polyethylene (HDPE) bottle with a polyester fiber coil, capped with a child-resistant closure. Each bottle contains 60 film-coated tablets. | 61958-1701-1 | Oval-shaped; orange; "100" on one side and "GSI" on the other side

STORAGE AND HANDLING

Store between 20–30 °C (68–86 °F) with excursions permitted 15–30 °C (59–86 °F).

- Dispense only in original container.
- Do not use if seal over bottle opening is broken or missing.

17 PATIENT COUNSELING INFORMATION

Advise the patient to read the FDA-approved patient labeling (Medication Guide).

Hepatotoxicity

Advise patients that Zydelig can cause significant elevations in liver enzymes, and that serial testing of serum liver tests (ALT, AST, and bilirubin) are recommended while taking Zydelig [see Warnings and Precautions (5.1)]. Advise patients to report symptoms of liver dysfunction including jaundice, bruising, abdominal pain, or bleeding.

Severe Diarrhea or Colitis

Advise patients that Zydelig may cause severe diarrhea or colitis and to notify their healthcare provider immediately if the number of bowel movements in a day increases by six or more [see Warnings and Precautions (5.2)].

Pneumonitis

Advise patients of the possibility of pneumonitis, and to report any new or worsening respiratory symptoms including cough or dyspnea [see Warnings and Precautions (5.3)].

Infections

Advise patients that Zydelig can cause serious infections that may be fatal. Advise patients to immediately report symptoms of infection (e.g. pyrexia) [see Warnings and Precautions (5.4)].

Intestinal Perforation

Advise patients of the possibility for intestinal perforation and to notify their healthcare provider immediately if they experience severe abdominal pain [see Warnings and Precautions (5.5)].

Severe Cutaneous Reactions

Advise patients that Zydelig may cause severe cutaneous reactions and to notify their healthcare provider immediately if they develop a severe skin reaction [see Warnings and Precautions (5.6)].

Hypersensitivity Reactions

Advise patients that anaphylaxis can occur during treatment with Zydelig and to notify their healthcare provider immediately if they experience a hypersensitivity reaction, including anaphylaxis [see Warnings and Precautions (5.7)].

Neutropenia

Advise patients of the need for periodic monitoring of blood counts. Advise patients to notify their healthcare provider immediately if they develop a fever or any signs of infection [see Warnings and Precautions (5.8)].

Embryo-Fetal Toxicity

Advise pregnant women of the potential risk to a fetus. Advise females of reproductive potential to inform their healthcare provider of a known or suspected pregnancy [see Warnings and Precautions (5.9), Use in Specific Populations (8.1)].

Advise females of reproductive potential to use effective contraception during treatment with Zydelig and for 1 month after the last dose [see Use in Specific Populations (8.3)].

Advise males with female partners of reproductive potential to use effective contraception during treatment with Zydelig and for 3 months after receiving the last dose [see Use in Specific Populations (8.3)].

Lactation

Advise women not to breastfeed during treatment with Zydelig and for 1 month after the last dose [see Use in Specific Populations (8.2)].

Instructions for Taking Zydelig

Advise patients to take Zydelig exactly as prescribed and not to change their dose or to stop taking Zydelig unless they are told to do so by their healthcare provider. Zydelig may be taken with or without food. Zydelig tablets should be swallowed whole. Advise patients that if a dose of Zydelig is missed by less than 6 hours, to take the missed dose right away and take the next dose as usual. If a dose of Zydelig is missed by more than 6 hours, advise patients to wait and take the next dose at the usual time [see Dosage and Administration (2.1)].

Manufactured and distributed by:

Gilead Sciences, Inc.

Foster City, CA 94404

GSI and Zydelig are trademarks or registered trademarks of Gilead Sciences, Inc., or its related companies. All other trademarks referenced herein are the property of their respective owners.

© 2022 Gilead Sciences, Inc. All rights reserved.

205858-GS-006-PI

MEDICATION GUIDE
ZYDELIG® (zye-DEL-ig)
(idelalisib)
tablets

What is the most important information I should know about Zydelig?
Zydelig can cause serious side effects that can lead to death, including:

- Liver problems. Abnormal liver blood test results are common during treatment with Zydelig. Zydelig can cause severe liver problems. Your healthcare provider will do blood tests before and during your treatment with Zydelig to check for liver problems. Tell your healthcare provider right away if you get any of the following symptoms of liver problems:
  - yellowing of your skin or the white part of your eyes (jaundice)
  - dark or brown (tea colored) urine
  - pain in the upper right side of your stomach area (abdomen)
  - bleeding or bruising more easily than normal

- Severe diarrhea. Diarrhea is common during treatment with Zydelig and can sometimes be severe. Tell your healthcare provider right away if the number of bowel movements you have in a day increases by six or more. Ask your healthcare provider about medicines you can take to treat your diarrhea.
- Lung problems (pneumonitis). Your healthcare provider may do tests to check your lungs if you have breathing problems during treatment with Zydelig. Tell your healthcare provider right away if you get new or worsening cough, shortness of breath, difficulty breathing, or wheezing. Your healthcare provider may treat you with a corticosteroid medicine if you develop lung problems.
- Infections. Zydelig can cause serious infections that may lead to death. Tell your healthcare provider right away if you have a fever or any signs of an infection during treatment with Zydelig.
- Tear in intestinal wall (perforation). Tell your healthcare provider or get medical help right away if you get new or worsening stomach area (abdomen) pain, chills, fever, nausea, or vomiting.
- Severe skin reactions. Tell your healthcare provider right away if you get any of the following symptoms during treatment with Zydelig:
  - painful sores or ulcers on your skin, lips, or in your mouth
  - severe rash with blisters or peeling skin
  - rash with itching
  - fever
  - enlarged lymph nodes

If you have any of the above serious side effects during treatment with Zydelig, your healthcare provider may completely stop your treatment, stop your treatment for a period of time, or change your dose of Zydelig.
See "What are the possible side effects of Zydelig?" for more information about side effects.

What is Zydelig?
Zydelig is a prescription medicine used to treat people with chronic lymphocytic leukemia (CLL), in combination with rituximab, when CLL comes back after prior cancer treatment and when rituximab treatment alone may be used due to other health problems.
Zydelig should not be used as the first medicine to treat anyone, including people with CLL, small lymphocytic lymphoma (SLL), follicular lymphoma (FL), and other slow growing (indolent) non-Hodgkin lymphomas.
Zydelig should not be used in combination with bendamustine and rituximab, or in combination with rituximab to treat people with FL, SLL, and other indolent non-Hodgkin lymphomas.
It is not known if Zydelig is safe and effective in children.

Do not take Zydelig if you:

- have had a serious allergic reaction to idelalisib.
- have had a severe skin reaction called toxic epidermal necrolysis (TEN) to any drug.

Before taking Zydelig, tell your healthcare provider about all of your medical conditions, including if you:

- have liver problems
- have lung problems
- have an infection
- are pregnant or plan to become pregnant. Zydelig may harm your unborn baby. Females who are able to become pregnant should have a pregnancy test before starting treatment with Zydelig.
  - Females who are able to become pregnant should use effective birth control (contraception) during treatment with Zydelig and for 1 month after the last dose of Zydelig. Talk to your healthcare provider about birth control methods that may be right for you. Tell your healthcare provider right away if you become pregnant or think you are pregnant during treatment with Zydelig.
  - Males with female partners who are able to become pregnant should use effective birth control (contraception) during treatment with Zydelig and for 3 months after the last dose.
- are breastfeeding or plan to breastfeed. It is not known if Zydelig passes into your breast milk. Do not breastfeed during your treatment with Zydelig and for 1 month after the last dose.

Tell your healthcare provider about all the medicines you take, including prescription and over-the-counter medicines, vitamins, and herbal supplements. Zydelig and certain other medicines may affect each other. Know the medicines you take. Keep a list of your medicines and show it to your healthcare provider and pharmacist when you get a new medicine.

How should I take Zydelig?

- Take Zydelig exactly as your healthcare provider tells you to take it.
- Your healthcare provider may change your dose of Zydelig or tell you to stop taking Zydelig. Do not change your dose or stop taking Zydelig without first talking to your healthcare provider.
- Take Zydelig 2 times a day.
- You may take Zydelig with or without food.
- Take Zydelig tablets whole.
- Do not miss a dose of Zydelig. If you miss a dose of Zydelig by less than 6 hours, take the missed dose right away. Then take your next dose as usual. If you miss a dose of Zydelig by more than 6 hours, wait and take the next dose of Zydelig at your usual time.

What are the possible side effects of Zydelig?
Zydelig can cause serious side effects, including:

- See "What is the most important information I should know about Zydelig?"
- Serious allergic reactions, including a severe reaction known as anaphylaxis. Tell your healthcare provider or get medical help right away if you have signs or symptoms of a serious allergic reaction during treatment with Zydelig, including:

- swelling of the face, lips, or tongue
- trouble breathing or swallowing
- feeling dizzy or faint

- rash or hives
- cough
- a fast heartbeat

- Low white blood cell count (neutropenia). Neutropenia is common during treatment with Zydelig and can sometimes be severe. Your healthcare provider will check your blood counts regularly during treatment with Zydelig. Tell your healthcare provider right away if you have a fever or any signs of an infection during treatment with Zydelig.

The most common side effects of Zydelig when used in combination with rituximab include:

- pneumonia
- fever
- tiredness

- rash
- cough
- nausea

Tell your healthcare provider if you have any side effect that bothers you or that does not go away.
These are not all the possible side effects of Zydelig. Call your doctor for medical advice about side effects. You may report side effects to FDA at 1-800-FDA-1088.

How should I store Zydelig?

- Store Zydelig between 68°F to 86°F (20°C to 30°C).
- Keep Zydelig in its original container.
- Do not use Zydelig if the seal over the bottle opening is broken or missing.

Keep Zydelig and all medicines out of reach of children.

General information about the safe and effective use of Zydelig.
Medicines are sometimes prescribed for purposes other than those listed in a Medication Guide. Do not use Zydelig for a condition for which it was not prescribed. Do not give Zydelig to other people, even if they have the same symptoms you have. It may harm them. You can ask your healthcare provider or pharmacist for information about Zydelig that is written for health professionals.

What are the ingredients in Zydelig?
Active ingredient: idelalisib
Inactive ingredients: microcrystalline cellulose, hydroxypropyl cellulose, croscarmellose sodium, sodium starch glycolate, and magnesium stearate. The tablet coating contains polyethylene glycol, talc, polyvinyl alcohol, titanium dioxide and FD&C Yellow #6 or Sunset Yellow FCF Aluminum Lake (for the 100 mg tablet) and red iron oxide (for the 150 mg tablet).
Manufactured and distributed by: Gilead Sciences, Inc. Foster City, CA 94404
©2022 Gilead Sciences, Inc. All rights reserved
For more information, call 1-800-445-3235 or go to www.Zydelig.com.
205858-GS-005-MG

This Medication Guide has been approved by the U.S. Food and Drug Administration.

Revised: 2/2022

PRINCIPAL DISPLAY PANEL - 100 mg Tablet Bottle Label

NDC 61958-1701-1
60 tablets

Zydelig®
(idelalisib) Tablets

100 mg

DISPENSER: Each time Zydelig® is dispensed
give the patient the attached Medication Guide.

PRINCIPAL DISPLAY PANEL - 150 mg Tablet Bottle Label

NDC 61958-1702-1
60 tablets

Zydelig®
(idelalisib) Tablets

150 mg

DISPENSER: Each time Zydelig® is dispensed
give the patient the attached Medication Guide.